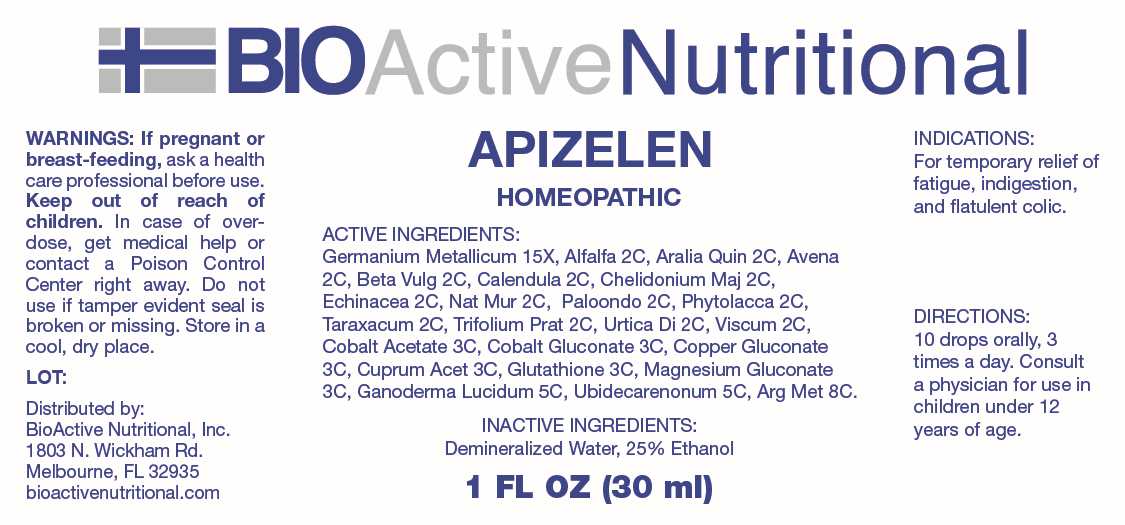 DRUG LABEL: Apizelen
NDC: 43857-0640 | Form: LIQUID
Manufacturer: BioActive Nutritional, Inc.
Category: homeopathic | Type: HUMAN OTC DRUG LABEL
Date: 20240515

ACTIVE INGREDIENTS: GERMANIUM 15 [hp_X]/1 mL; MEDICAGO SATIVA WHOLE 2 [hp_C]/1 mL; AMERICAN GINSENG 2 [hp_C]/1 mL; AVENA SATIVA FLOWERING TOP 2 [hp_C]/1 mL; BETA VULGARIS WHOLE 2 [hp_C]/1 mL; CALENDULA OFFICINALIS FLOWERING TOP 2 [hp_C]/1 mL; CHELIDONIUM MAJUS WHOLE 2 [hp_C]/1 mL; ECHINACEA ANGUSTIFOLIA WHOLE 2 [hp_C]/1 mL; SODIUM CHLORIDE 2 [hp_C]/1 mL; LARREA TRIDENTATA LEAF 2 [hp_C]/1 mL; PHYTOLACCA AMERICANA ROOT 2 [hp_C]/1 mL; TARAXACUM OFFICINALE 2 [hp_C]/1 mL; TRIFOLIUM PRATENSE FLOWER 2 [hp_C]/1 mL; URTICA DIOICA WHOLE 2 [hp_C]/1 mL; VISCUM ALBUM FRUITING TOP 2 [hp_C]/1 mL; COBALTOUS ACETATE 3 [hp_C]/1 mL; COBALTOUS GLUCONATE 3 [hp_C]/1 mL; COPPER GLUCONATE 3 [hp_C]/1 mL; CUPRIC ACETATE 3 [hp_C]/1 mL; GLUTATHIONE 3 [hp_C]/1 mL; MAGNESIUM GLUCONATE 3 [hp_C]/1 mL; REISHI 5 [hp_C]/1 mL; UBIDECARENONE 5 [hp_C]/1 mL; SILVER 8 [hp_C]/1 mL
INACTIVE INGREDIENTS: WATER; ALCOHOL

DRUG FACTS:

ACTIVE INGREDIENTS:

Germanium Metallicum 15X, Alfalfa 2C, Aralia Quinquefolia 2C, Avena Sativa 2C, Beta Vulgaris 2C, Calendula Officinalis 2C, Chelidonium Majus 2C, Echinacea (Angustifolia) 2C, Natrum Muriaticum 2C, Paloondo 2C, Phytolacca Decandra 2C, Taraxacum Officinale 2C, Trifolium Pratense 2C, Urtica Dioica 2C, Viscum Album 2C, Cobalt Acetate 3C, Cobalt Gluconate 3C, Copper Gluconate 3C, Cuprum Aceticum 3C, Glutathione 3C, Magnesium Gluconicum Dihydricum 3C, Ganoderma Lucidum 5C, Ubidecarenonum 5C, Argentum Metallicum 8C.

PURPOSE:

For temporary relief of fatigue, indigestion, and flatulent colic.

WARNINGS:

If pregnant or breast-feeding, ask a health care professional before use.

Keep out of reach of children. In case of overdose, get medical help or contact a Poison Control Center right away.

Do not use if tamper evident seal is broken or missing.

Store in cool, dry place.

KEEP OUT OF REACH OF CHILDREN:

In case of overdose, get medical help or contact a Poison Control Center right away.

DIRECTIONS:

10 drops orally, 3 times a day. Consult a physician for use in children under 12 years of age.

INDICATIONS:

For temporary relief of fatigue, indigestion, and flatulent colic.

INACTIVE INGREDIENTS:

Demineralized Water, 25% Ethanol

QUESTIONS:

Distributed by:
BioActive Nutritional, Inc.
1803 N. Wickham Rd.
Melbourne, FL 32935
bioactivenutritional.com

PACKAGE LABEL DISPLAY:

BIOActive Nutritional

APIZELEN

HOMEOPATHIC

1 FL OZ (30 ml)